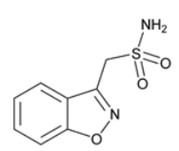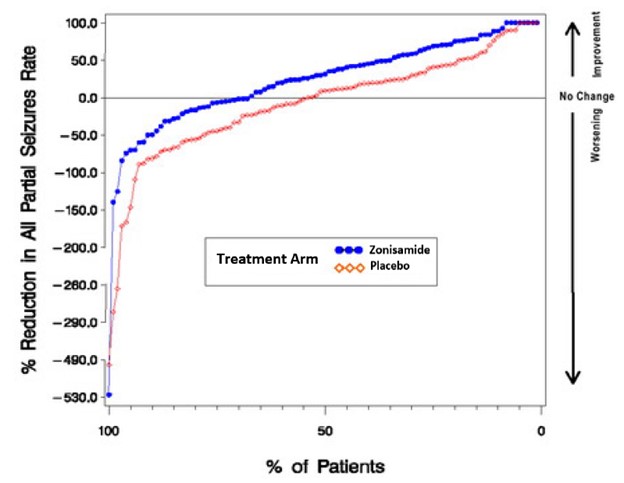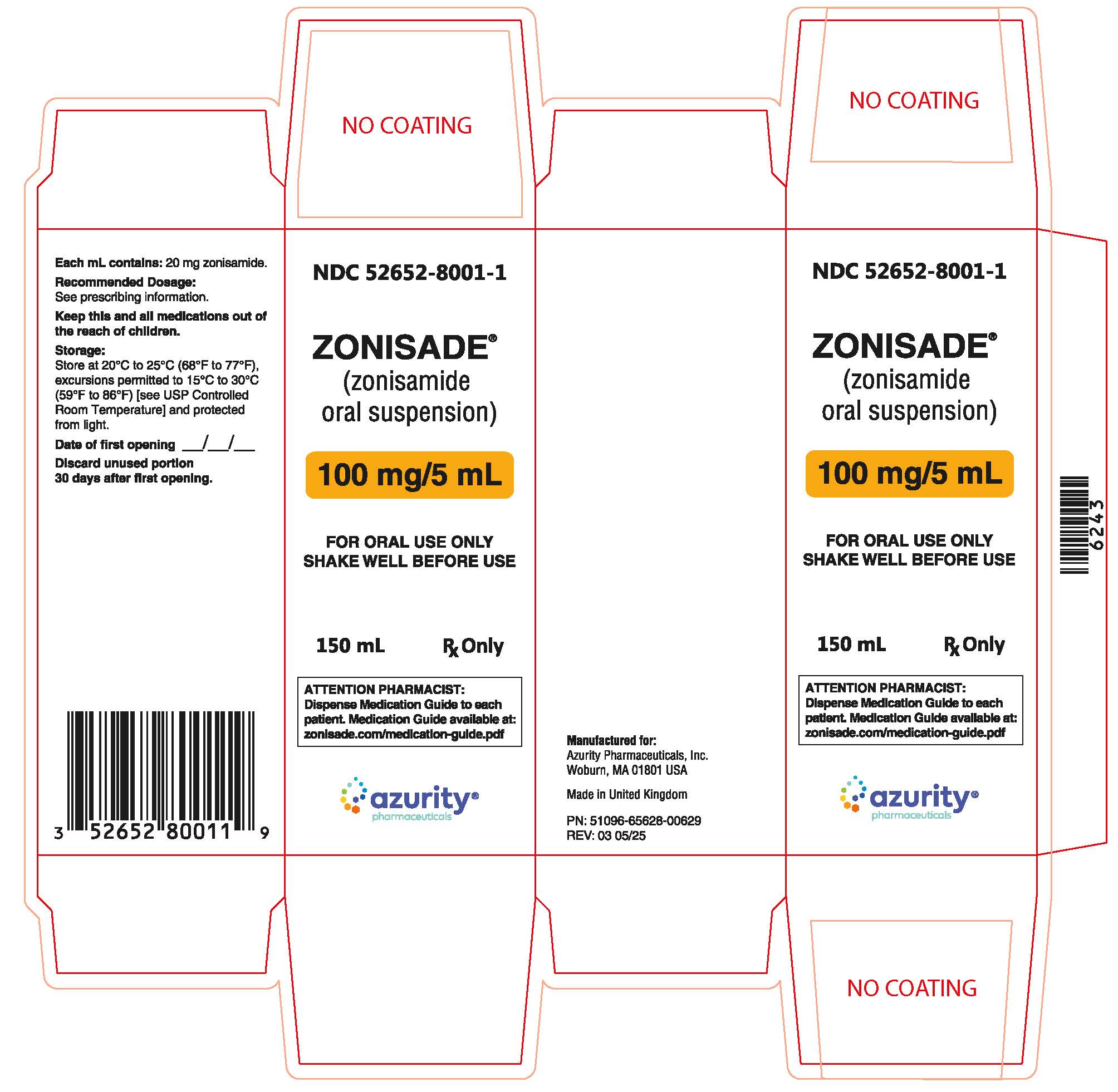 DRUG LABEL: ZONISADE
NDC: 52652-8001 | Form: SUSPENSION
Manufacturer: Azurity Pharmaceuticals, Inc.
Category: prescription | Type: Human Prescription Drug Label
Date: 20250908

ACTIVE INGREDIENTS: ZONISAMIDE 100 mg/5 mL
INACTIVE INGREDIENTS: CARBOXYMETHYLCELLULOSE SODIUM, UNSPECIFIED FORM; CITRIC ACID MONOHYDRATE; MICROCRYSTALLINE CELLULOSE; WATER; SODIUM BENZOATE; SUCRALOSE; TRISODIUM CITRATE DIHYDRATE; XANTHAN GUM

HIGHLIGHTS OF PRESCRIBING INFORMATION

These highlights do not include all the information needed to use ZONISADE® safely and effectively. See full prescribing information for ZONISADE®
ZONISADE® (zonisamide oral suspension)
Initial U.S. Approval: 2000

1 INDICATIONS AND USAGE

ZONISADE is indicated as adjunctive therapy for the treatment of partial-onset seizures in adults and pediatric patients 16 years of age and older (1).

2 DOSAGE AND ADMINISTRATION

- The recommended initial dosage of ZONISADE is 100 mg daily. The dosage may be increased by 100 mg daily every two weeks, based on clinical response and tolerability, to 400 mg daily. Patients who are tolerating ZONISADE at 400 mg daily and require further reduction of seizures may be increased up to a maximum dosage of 600 mg daily (2.2).
- ZONISADE is given orally and can be taken with or without food (2.2).

3 DOSAGE FORMS AND STRENGTHS

ZONISADE: 100 mg/5 mL (3).

4 CONTRAINDICATIONS

ZONISADE is contraindicated in patients who have demonstrated hypersensitivity to sulfonamides or zonisamide (4).

5 WARNINGS AND PRECAUTIONS

- Potentially Fatal Reactions to Sulfonamides: Fatalities have occurred as a result of severe reactions to sulfonamides (zonisamide is a sulfonamide) including Stevens-Johnson syndrome, toxic epidermal necrolysis, fulminant hepatic necrosis, agranulocytosis, aplastic anemia, and other blood dyscrasias (5.1).
- Serious Skin Reactions: Discontinue ZONISADE at the first sign of rash unless clearly not drug related (5.2).
- Serious Hematologic Events: Aplastic anemia and agranulocytosis have been reported with zonisamide treatment (5.3).
- Drug Reaction with Eosinophilia and Systemic Symptoms (DRESS)/Multi-Organ Hypersensitivity: DRESS, also known as multiorgan hypersensitivity, has occurred with zonisamide (5.4).
- Oligohidrosis and Hyperthermia in Pediatric Patients: Oligohidrosis, sometimes resulting in heat stroke and hospitalization, is seen in association with zonisamide in pediatric patients (5.5).
- Acute Myopia and Secondary Angle Closure Glaucoma: If occurs, primary treatment is discontinuation of ZONISADE (5.6).
- Suicidal Behavior and Ideation: Monitor patients for suicidal behavior or ideation (5.7).
- Metabolic Acidosis: Baseline and periodic measurement of serum bicarbonate is recommended; consider dose reduction or discontinuation if appropriate (5.8).
- Seizures on Withdrawal of Antiepileptic Drugs: Withdraw ZONISADE gradually (5.9).
- Teratogenicity: Based on animal data, may cause fetal harm. Advise females of reproductive potential of the potential risk to a fetus and to use an effective method of contraception during ZONISADE treatment and for one month after discontinuation (5.10, 8.1, 8.3).

6 ADVERSE REACTIONS

The most common adverse reactions with ZONISADE (an incidence at least 4% greater than placebo) in controlled clinical trials and shown in descending order of frequency were somnolence, anorexia, dizziness, ataxia, agitation/irritability, and difficulty with memory and/or concentration (6).

To report SUSPECTED ADVERSE REACTIONS, contact Azurity Pharmaceuticals, Inc., at 1-800-461-7449 or FDA at 1-800-FDA-1088 or www.fda.gov/medwatch.

7 DRUG INTERACTIONS

- ZONISADE should be used with caution if used in combination with alcohol or other CNS depressants (7.1).
- Concomitant use of ZONISADE with any other carbonic anhydrase inhibitor may increase the severity of metabolic acidosis and may also increase the risk of kidney stone formation (7.2).

FULL PRESCRIBING INFORMATION

1 INDICATIONS AND USAGE

ZONISADE is indicated as adjunctive therapy for the treatment of partial-onset seizures in adults and pediatric patients 16 years and older.

2 DOSAGE AND ADMINISTRATION

2.1 Recommended Assessments for Safety

To assess for metabolic acidosis, obtain baseline serum bicarbonate prior to initiating ZONISADE, and obtain periodic serum bicarbonate during treatment [see Warnings and Precautions (5.8)].

2.2 Recommended Dosage

Administer ZONISADE once or twice daily with or without food.

The recommended initial dosage of ZONISADE is 100 mg daily. The dosage may be increased by 100 mg daily every two weeks, based on clinical response and tolerability, to 400 mg daily. Patients who are tolerating ZONISADE at 400 mg daily and require further reduction of seizures may be increased up to a maximum dosage of 600 mg daily. However, evidence from controlled trials shows no suggestion of increasing response above 400 mg/day [see Clinical Studies (14)].

2.3 Important Administration Information

Shake well before every administration. To administer ZONISADE directly into the mouth, it is important that ZONISADE be measured with an accurate measuring device [see Overdosage (10)]. A household teaspoon is not an accurate measuring device. A pharmacist will provide an appropriate device and instructions for measuring the correct dose.

Administer ZONISADE orally with or without food.

Discard unused portion of ZONISADE 30 days after first opening the bottle.

2.4 Discontinuation of ZONISADE

When discontinuing ZONISADE, the dose should be decreased gradually. As with most antiepileptic drugs, avoid abrupt discontinuation, when possible, to minimize the risk of increased seizure frequency and status epilepticus [see Warnings and Precautions (5.9)].

3 DOSAGE FORMS AND STRENGTHS

Oral suspension: 100 mg/5 mL of zonisamide as a white to off-white, strawberry flavored liquid.

4 CONTRAINDICATIONS

ZONISADE is contraindicated in patients who have demonstrated hypersensitivity to sulfonamides or zonisamide.

5 WARNINGS AND PRECAUTIONS

5.1 Potentially Fatal Reactions to Sulfonamides

Fatalities have occurred as a result of severe reactions to sulfonamides (zonisamide is a sulfonamide) including Stevens-Johnson syndrome, toxic epidermal necrolysis, fulminant hepatic necrosis, agranulocytosis, aplastic anemia, and other blood dyscrasias [see Warnings and Precautions (5.2, 5.3, 5.4)]. Such reactions may occur when a sulfonamide is readministered irrespective of the route of administration. If signs of hypersensitivity or other serious reactions occur, discontinue ZONISADE immediately. Specific experience with sulfonamide-type adverse reaction to zonisamide is described below.

5.2 Serious Skin Reactions

Seven deaths from severe rash [i.e., Stevens-Johnson syndrome (SJS) and toxic epidermal necrolysis (TEN)] were reported in the first 11 years of marketing in Japan. All of the patients were receiving other drugs in addition to zonisamide. In postmarketing experience from Japan, a total of 49 cases of SJS or TEN have been reported, a reporting rate of 46 per million patient-years of exposure. Although this rate is greater than background, it is probably an underestimate of the true incidence because of under-reporting. There were no confirmed cases of SJS or TEN in the US, European, or Japanese development programs.

In the US and European randomized controlled trials [see Clinical Studies (14)], 6 of 269 (2.2%) patients who received zonisamide discontinued treatment because of rash compared to no patients who received placebo. Across all trials during the US and European development, rash that led to discontinuation of zonisamide was reported in 1.4% of patients (12.0 events per 1000 patient-years of exposure). During Japanese development, serious rash or rash that led to discontinuation of zonisamide was reported in 2.0% of patients (27.8 events per 1000 patient-years). Rash usually occurred early in treatment, with 85% reported within 16 weeks in the US and European studies and 90% reported within two weeks in the Japanese studies. There was no apparent relationship of dose to the occurrence of rash.

Discontinue ZONISADE at the first sign of rash, unless the rash is clearly not drug-related. If signs or symptoms suggest SJS/TEN, use of ZONISADE should not be resumed and alternative therapy should be considered.

5.3 Serious Hematologic Events

Two confirmed cases of aplastic anemia and one confirmed case of agranulocytosis were reported in the first 11 years of marketing in Japan, rates greater than generally accepted background rates. There were no cases of aplastic anemia and two confirmed cases of agranulocytosis in the US, European, or Japanese development programs. There is inadequate information to assess the relationship, if any, between dose and duration of treatment and these events.

5.4 Drug Reaction with Eosinophilia and Systemic Symptoms (DRESS)/Multi-Organ Hypersensitivity

Drug Reaction with Eosinophilia and Systemic Symptoms (DRESS), also known as multi-organ hypersensitivity, has occurred with zonisamide, the active ingredient in ZONISADE. Some of these events have been fatal or life-threatening. DRESS typically, although not exclusively, presents with fever, rash, lymphadenopathy and/or facial swelling, in association with other organ system involvement, such as hepatitis, nephritis, hematologic abnormalities, myocarditis, or myositis, sometimes resembling an acute viral infection. Eosinophilia is often present. This disorder is variable in its expression, and other organ systems not noted here may be involved. It is important to note that early manifestations of hypersensitivity (e.g., fever, lymphadenopathy) may be present even though rash is not evident.

If such signs or symptoms are present, the patient should be evaluated immediately. ZONISADE should be discontinued if an alternative etiology for the signs or symptoms cannot be established.

5.5 Oligohidrosis and Hyperthermia in Pediatric Patients

ZONISADE is not approved for use in patients below 16 years of age.

Oligohidrosis, sometimes resulting in heat stroke and hospitalization, is seen in association with zonisamide in pediatric patients.

During the pre-approval development program in Japan, one case of oligohidrosis was reported in 403 pediatric patients, an incidence of 1 case per 285 patient-years of exposure. While there were no cases reported in the US or European development programs, fewer than 100 pediatric patients participated in these trials.

In the first 11 years of marketing in Japan, 38 cases were reported, an estimated reporting rate of about 1 case per 10,000 patient-years of exposure. In the first year of marketing in the US, 2 cases were reported, an estimated reporting rate of about 12 cases per 10,000 patient-years of exposure. These rates are underestimates of the true incidence because of under-reporting. There has also been one report of heat stroke in an 18-year-old patient in the US.

Decreased sweating and an elevation in body temperature above normal characterized these cases. Many cases were reported after exposure to elevated environmental temperatures. Heat stroke, requiring hospitalization, was diagnosed in some cases.

Pediatric patients appear to be at an increased risk for zonisamide-associated oligohidrosis and hyperthermia. Patients, especially pediatric patients, treated with ZONISADE should be monitored closely for evidence of decreased sweating and increased body temperature, especially in warm or hot weather. Caution should be used when ZONISADE is prescribed with other drugs that predispose patients to heat-related disorders; these drugs include, but are not limited to, carbonic anhydrase inhibitors and drugs with anticholinergic activity.

5.6 Acute Myopia and Secondary Angle Closure Glaucoma

Acute myopia and secondary angle closure glaucoma have been reported in patients receiving zonisamide, the active ingredient in ZONISADE. Elevated intraocular pressure can lead to serious sequelae, including permanent vision loss, if left untreated.

Symptoms in reported cases have included acute onset of decreased visual acuity and/or ocular pain. Ophthalmologic findings can include myopia, anterior chamber shallowing, ocular hyperemia (redness), and increased intraocular pressure. Mydriasis may or may not be present. This syndrome may be associated with ciliochoroidal effusion resulting in anterior displacement of the lens and iris, with secondary angle closure glaucoma. Symptoms typically occur within one month after initiating zonisamide therapy. In contrast to primary narrow angle glaucoma, which is rare under 40 years of age, secondary angle closure glaucoma associated with zonisamide has been reported both in pediatric patients and in adults. ZONISADE is not approved for use in patients below 16 years of age. The primary treatment to reverse symptoms is discontinuation of ZONISADE as rapidly as possible, according to the judgment of the treating physician. Other therapeutic measures, in conjunction with discontinuation of ZONISADE, may be helpful. Myopia and secondary angle closure glaucoma usually resolve or improve after discontinuation of zonisamide.

5.7 Suicidal Behavior and Ideation

Antiepileptic drugs (AEDs), including ZONISADE, increase the risk of suicidal thoughts or behavior in patients taking these drugs for any indication. Patients treated with any AED for any indication should be monitored for the emergence or worsening of depression, suicidal thoughts or behavior, and/or any unusual changes in mood or behavior.

Pooled analyses of 199 placebo-controlled clinical trials (mono- and adjunctive therapy) of 11 different AEDs showed that patients randomized to one of the AEDs had approximately twice the risk (adjusted Relative Risk 1.8, 95% CI:1.2, 2.7) of suicidal thinking or behavior compared to patients randomized to placebo. In these trials, which had a median treatment duration of 12 weeks, the estimated incidence rate of suicidal behavior or ideation among 27,863 AED-treated patients was 0.43%, compared to 0.24% among 16,029 placebo-treated patients, representing an increase of approximately one case of suicidal thinking or behavior for every 530 patients treated. There were four suicides in drug-treated patients in the trials and none in placebo-treated patients, but the number is too small to allow any conclusion about drug effect on suicide.

The increased risk of suicidal thoughts or behavior with AEDs was observed as early as one week after starting drug treatment with AEDs and persisted for the duration of treatment assessed. Because most trials included in the analysis did not extend beyond 24 weeks, the risk of suicidal thoughts or behavior beyond 24 weeks could not be assessed.

The risk of suicidal thoughts or behavior was generally consistent among drugs in the data analyzed. The finding of increased risk with AEDs of varying mechanisms of action and across a range of indications suggests that the risk applies to all AEDs used for any indication. The risk did not vary substantially by age (5-100 years) in the clinical trials analyzed.

Table 1 shows absolute and relative risk by indication for all evaluated AEDs.

Table 1. Risk by Indication for Antiepileptic Drugs in the Pooled Analysis
Indication | Placebo Patients with Events Per 1000 Patients | Drug Patients with Events Per 1000 Patients | Relative Risk: Incidence of Events in Drug Patients/Incidence in Placebo Patients | Risk Difference: Additional Drug Patients with Events Per 1000 Patients
Epilepsy | 1.0 | 3.4 | 3.5 | 2.4
Psychiatric | 5.7 | 8.5 | 1.5 | 2.9
Other | 1.0 | 1.8 | 1.9 | 0.9
Total | 2.4 | 4.3 | 1.8 | 1.9

The relative risk for suicidal thoughts or behavior was higher in clinical trials for epilepsy than in clinical trials for psychiatric or other conditions, but the absolute risk differences were similar for the epilepsy and psychiatric indications.

Anyone considering prescribing ZONISADE or any other AED must balance the risk of suicidal thoughts or behavior with the risk of untreated illness. Epilepsy and many other illnesses for which AEDs are prescribed are themselves associated with morbidity and mortality and an increased risk of suicidal thoughts and behavior. Should suicidal thoughts and behavior emerge during treatment, the prescriber needs to consider whether the emergence of these symptoms in any given patient may be related to the illness being treated.

5.8 Metabolic Acidosis

Zonisamide causes hyperchloremic, non-anion gap, metabolic acidosis (i.e., decreased serum bicarbonate below the normal reference range in the absence of chronic respiratory alkalosis). This metabolic acidosis is caused by renal bicarbonate loss due to the inhibitory effect of zonisamide on carbonic anhydrase. Generally, zonisamide-induced metabolic acidosis occurs early in treatment, but it can develop at any time during treatment. Metabolic acidosis generally appears dose-dependent and can occur at doses as low as 25 mg daily.

Conditions or therapies that predispose to acidosis (such as renal disease, severe respiratory disorders, status epilepticus, diarrhea, ketogenic diet, or specific drugs) may be additive to the bicarbonate lowering effects of zonisamide.

Some manifestations of acute or chronic metabolic acidosis include hyperventilation, nonspecific symptoms such as fatigue and anorexia, or more severe sequelae including cardiac arrhythmias or stupor. Chronic, untreated, metabolic acidosis may increase the risk for nephrolithiasis or nephrocalcinosis. Nephrolithiasis has been observed in the clinical development program in 4% of adults treated with zonisamide, has also been detected by renal ultrasound in 8% of pediatric treated patients who had at least one ultrasound prospectively collected, and was reported as an adverse event in 3% (4/133) of pediatric patients [see Warnings and Precautions (5.15)]. Metabolic acidosis can also increase the risk for hyperammonemia, particularly in the presence of drugs which can cause hyperammonemia.

Chronic, untreated metabolic acidosis may result in osteomalacia (referred to as rickets in pediatric patients) and/or osteoporosis with an increased risk for fracture. Of potential relevance, zonisamide treatment was associated with reductions in serum phosphorus and increases in serum alkaline phosphatase, changes that may be related to metabolic acidosis and osteomalacia.

Chronic, untreated metabolic acidosis in pediatric patients may reduce growth rates. A reduction in growth rate may eventually decrease the maximal height achieved. The effect of zonisamide on growth and bone-related sequelae has not been systematically investigated. ZONISADE is not approved for use in patients below 16 years of age.

Serum bicarbonate was not measured in the adjunctive controlled trials of adults with epilepsy. However, serum bicarbonate was studied in three clinical trials for indications which have not been approved: a placebo-controlled trial for migraine prophylaxis in adults, a controlled trial for monotherapy in epilepsy in adults, and an open label trial for adjunctive treatment of epilepsy in pediatric patients (3-16 years). In adults, mean serum bicarbonate reductions ranged from approximately 2 mEq/L at daily doses of 100 mg to nearly 4 mEq/L at daily doses of 300 mg. In pediatric patients, mean serum bicarbonate reductions ranged from approximately 2 mEq/L at daily doses from above 100 mg up to 300 mg, to nearly 4 mEq/L at daily doses from above 400 mg up to 600 mg.

In two controlled studies in adults, the incidence of a persistent treatment-emergent decrease in serum bicarbonate to less than 20 mEq/L (observed at 2 or more consecutive visits or the final visit) was dose-related at relatively low zonisamide doses. In the monotherapy trial of epilepsy, the incidence of a persistent treatment-emergent decrease in serum bicarbonate was 21% for daily zonisamide doses of 25 mg or 100 mg, and was 43% at a daily dose of 300 mg. In a placebo-controlled trial for prophylaxis of migraine, the incidence of a persistent treatment-emergent decrease in serum bicarbonate was 7% for placebo, 29% for 150 mg daily, and 34% for 300 mg daily. The incidence of persistent markedly abnormally low serum bicarbonate (decrease to less than 17 mEq/L and more than 5 mEq/L from a pretreatment value of at least 20 mEq/L) in these controlled trials was 2% or less.

In the pediatric study, the incidence of persistent, treatment-emergent decreases in serum bicarbonate to levels less than 20 mEq/L was 52% at doses up to 100 mg daily, was 90% for a wide range of doses up to 600 mg daily, and generally appeared to increase with higher doses. The incidence of a persistent markedly abnormally low serum bicarbonate value was 4% at doses up to 100 mg daily, was 18% for a wide range of doses up to 600 mg daily, and generally appeared to increase with higher doses. Some patients experienced moderately severe serum bicarbonate decrements down to a level as low as 10 mEq/L.

The relatively high frequencies of varying severities of metabolic acidosis observed in this study of pediatric patients (compared to the frequency and severity observed in various clinical trial development programs in adults) suggest that pediatric patients may be more likely to develop metabolic acidosis than adults.

Measurement of baseline and periodic serum bicarbonate during treatment is recommended. If metabolic acidosis develops and persists, consideration should be given to reducing the dose or discontinuing ZONISADE (using dose tapering). If the decision is made to continue patients on ZONISADE in the face of persistent acidosis, alkali treatment should be considered.

5.9 Seizures on Withdrawal of Antiepileptic Drugs

As with most antiepileptic drugs, ZONISADE should generally be withdrawn gradually because of the risk of increased seizure frequency and status epilepticus [see Dosage and Administration (2.3)]. However, if withdrawal is needed because of a serious adverse event, rapid discontinuation can be considered. In these situations, appropriate monitoring is recommended.

5.10 Teratogenicity

Women of childbearing potential who are given ZONISADE should be advised to use effective contraception. Zonisamide produced fetal malformations in mice, rats, and dogs and was embryolethal in monkeys when administered during the period of organogenesis. A variety of fetal abnormalities, including cardiovascular defects and embryofetal deaths, occurred at maternal plasma levels similar to or lower than therapeutic levels in humans. These findings suggest that the use of zonisamide during pregnancy in humans may present a significant risk to the fetus [see Use in Specific Populations (8.1)].

Although human data to confirm findings in animals is limited, ZONISADE should be used during pregnancy only if the potential benefit justifies the potential risk to the fetus.

5.11 Cognitive/Neuropsychiatric Adverse Reactions

Use of zonisamide was frequently associated with central nervous system-related adverse reactions [see Adverse Reactions (6.1)]. The most significant of these can be classified into three general categories: 1) psychiatric symptoms, including depression and psychosis, 2) cognitive dysfunction, and 3) somnolence or fatigue.

Psychiatric Symptoms

In placebo-controlled trials, 2.2% of patients discontinued zonisamide or were hospitalized for depression compared to 0.4% of placebo patients. Among all epilepsy patients treated with zonisamide, 1.4% were discontinued and 1.0% were hospitalized because of reported depression or suicide attempts. In placebo-controlled trials, 2.2% of patients discontinued zonisamide or were hospitalized because of psychosis or psychosis-related symptoms compared to no patients who received placebo. Among all epilepsy patients treated with zonisamide, 0.9% discontinued treatment and 1.4% were hospitalized because of reported psychosis or related symptoms.

Cognitive Dysfunction

Zonisamide, the active ingredient in ZONISADE, causes adverse reactions related to cognitive dysfunction (e.g., psychomotor slowing, difficulty with concentration, and speech or language problems, in particular, word-finding difficulties). In placebo-controlled trials with zonisamide, psychomotor slowing and difficulty with concentration occurred in the first month of treatment and were associated with doses above 300 mg/day. Speech and language problems tended to occur after 6–10 weeks of treatment and at doses above 300 mg/day. Although in most cases these events were of mild to moderate severity, they at times led to withdrawal from treatment.

Somnolence and Fatigue

Somnolence and fatigue were frequently reported CNS adverse events during clinical trials with zonisamide. Although in most cases these events were of mild to moderate severity, they led to withdrawal from treatment in 0.2% of the patients enrolled in controlled trials. Somnolence and fatigue tended to occur within the first month of treatment. Somnolence and fatigue occurred most frequently at doses of 300–500 mg/day.

Risk Amelioration

Prescribers should advise patients against engaging in hazardous activities requiring mental alertness, such as operating motor vehicles or dangerous machinery, until the effect of ZONISADE is known. Patients should be carefully observed for signs of central nervous system (CNS) depression, such as somnolence and sedation, when ZONISADE is used with other drugs with sedative properties because of potential additive effects.

5.12 Hyperammonemia and Encephalopathy

Hyperammonemia and encephalopathy have been reported with the postmarketing use of zonisamide. Zonisamide, the active ingredient in ZONISADE, treatment inhibits carbonic anhydrase activity, which may cause metabolic acidosis that is associated with an increased risk for developing hyperammonemia. Hyperammonemia resulting from zonisamide can also be asymptomatic.

The risks of hyperammonemia and various manifestations of encephalopathy may be increased in patients treated with zonisamide and concomitantly taking other medications that can cause hyperammonemia, including valproic acid or topiramate [see Warnings and Precautions (5)]. Patients with inborn errors of metabolism or reduced hepatic mitochondrial activity may be at an increased risk for hyperammonemia with or without encephalopathy and this risk may be increased by zonisamide use.

Measure serum ammonia concentration if signs or symptoms (e.g., unexplained change in mental status, vomiting, or lethargy) of encephalopathy occur. Hyperammonemia resulting from zonisamide resolves when zonisamide is discontinued. Hyperammonemia from zonisamide may resolve or decrease in severity with a decrease of the daily dose.

5.13 Kidney Stones

Zonisamide, the active ingredient in ZONISADE, may cause kidney stones. Among 991 patients treated during the development of zonisamide, 40 patients (4.0%) with epilepsy receiving zonisamide developed clinically possible or confirmed kidney stones (e.g., clinical symptomatology, sonography, etc.), at rate of 34 per 1000 patient-years of exposure (40 patients with 1168 years of exposure). Of these, 12 were symptomatic, and 28 were described as possible kidney stones based on sonographic detection. In nine patients, the diagnosis was confirmed by a passage of a stone or by a definitive sonographic finding. The rate of occurrence of kidney stones was 28.7 per 1000 patient-years of exposure in the first six months, 62.6 per 1000 patient-years of exposure between 6 and 12 months, and 24.3 per 1000 patient-years of exposure after 12 months of use. There are no normative sonographic data available for either the general population or patients with epilepsy. Although the clinical significance of the sonographic findings may not be certain, the development of nephrolithiasis may be related to metabolic acidosis [see Warnings and Precautions (5.8)]. The analyzed stones were composed of calcium or urate salts. In general, increasing fluid intake and urine output can help reduce the risk of stone formation, particularly in those with predisposing risk factors. It is unknown, however, whether these measures will reduce the risk of stone formation in patients treated with ZONISADE.
Although not approved in pediatric patients, sonographic findings consistent with nephrolithiasis were also detected in 8% of a subset of zonisamide treated pediatric patients who had at least one renal ultrasound prospectively performed in a clinical development program investigating open-label treatment. The incidence of kidney stone as an adverse event was 3% [see Warnings and Precautions (5.8)].

5.14 Effect on Renal Function

Zonisamide, the active ingredient in ZONISADE, can have an effect on renal function. In several clinical studies, zonisamide was associated with a statistically significant 8% mean increase from baseline of serum creatinine and blood urea nitrogen (BUN) compared to essentially no change in the placebo patients. The increase appeared to persist over time but was not progressive; this has been interpreted as an effect on glomerular filtration rate (GFR). There were no episodes of unexplained acute renal failure in clinical development in the US, Europe, or Japan. The decrease in GFR appeared within the first 4 weeks of treatment. In a 30-day study, the GFR returned to baseline within 2–3 weeks of drug discontinuation. There is no information about reversibility, after drug discontinuation, of the effects on GFR after long-term use. ZONISADE should be discontinued in patients who develop acute renal failure or a clinically significant sustained increase in the creatinine/BUN concentration. Avoid use of ZONISADE in patients with renal failure (estimated GFR < 50 mL/min) since there is insufficient experience concerning drug dosing and toxicity [see Use in Specific Populations (8.6)]. Consideration should be given to monitoring renal function periodically.

5.15 Status Epilepticus

Estimates of the incidence of treatment emergent status epilepticus in patients treated with zonisamide, the active ingredient in ZONISADE, are difficult because a standard definition was not employed. Nonetheless, in controlled trials, 1.1% of patients treated with zonisamide had an event labeled as status epilepticus compared to none of the patients treated with placebo. Among patients treated with zonisamide across all epilepsy studies (controlled and uncontrolled), 1.0% of patients had an event reported as status epilepticus.

6 ADVERSE REACTIONS

The following clinically signification adverse reactions are described elsewhere in the labeling:

- Potentially Fatal Reactions to Sulfonamides [see Warnings and Precautions (5.1)]
- Serious Skin Reactions [see Warnings and Precautions (5.2)]
- Serious Hematologic Events [see Warnings and Precautions (5.3)]
- Drug Reaction with Eosinophilia and Systemic Symptoms (DRESS)/Multi-Organ Hypersensitivity [see Warnings and Precautions (5.4)]
- Oligohidrosis and Hyperthermia in Pediatric Patients [see Warnings and Precautions (5.5)]
- Acute Myopia and Secondary Angle Closure Glaucoma [see Warnings and Precautions (5.6)]
- Suicidal Behavior and Ideation [see Warnings and Precautions (5.7)]
- Metabolic Acidosis [see Warnings and Precautions (5.8)]
- Seizures on Withdrawal of Antiepileptic Drugs [see Warnings and Precautions (5.9)]
- Teratogenicity [see Warnings and Precautions (5.10)]
- Cognitive/Neuropsychiatric Adverse Reactions [see Warnings and Precautions (5.11)]
- Hyperammonemia and Encephalopathy [see Warnings and Precautions (5.12)]
- Kidney Stones [see Warnings and Precautions (5.13)]
- Effect on Renal Function [see Warnings and Precautions (5.14)]
- Status Epilepticus [see Warnings and Precautions (5.15)]

6.1 Clinical Trials Experience

Because clinical trials are conducted under widely varying conditions, adverse reaction rates observed in the clinical trials of a drug cannot be directly compared to rates in the clinical trials of another drug and may not reflect the rates observed in practice.

Adverse Reactions in Placebo-Controlled Trials with Zonisamide Capsules [see Clinical Studies (14)]

The most common adverse reactions with zonisamide capsules (an incidence at least 4% greater than placebo) in controlled clinical trials and shown in descending order of frequency were somnolence, anorexia, dizziness, ataxia, agitation/irritability, and difficulty with memory and/or concentration.

In controlled clinical trials, 12% of patients receiving zonisamide as adjunctive therapy discontinued because of an adverse reaction compared to 6% receiving placebo. Approximately 21% of the 1,336 patients with epilepsy who received zonisamide in clinical studies discontinued treatment because of an adverse reaction. The most common adverse reactions leading to discontinuation were somnolence, fatigue and/or ataxia (6%), anorexia (3%), difficulty concentrating (2%), difficulty with memory, mental slowing, nausea/vomiting (2%), and weight loss (1%). Many of these adverse reactions were dose-related [see Warnings and Precautions (5)].

Table 2 lists adverse reactions that occurred in at least 2% of patients treated with zonisamide capsules in controlled clinical trials that were numerically more common in the zonisamide group. In these studies, either zonisamide or placebo was added to the patient's current AED therapy.

Table 2. Adverse Reactions that Occurred in at least 2% of Patients Treated with Zonisamide Capsules and More Frequently than in Patients who Received Placebo in Placebo-Controlled, Adjunctive Trials
BODY SYSTEM/Adverse Reaction | Zonisamide Capsules (n=269) % | Placebo (n=230) %
BODY AS A WHOLE
Headache | 10 | 8
Abdominal Pain | 6 | 3
Flu Syndrome | 4 | 3
DIGESTIVE
Anorexia | 13 | 6
Nausea | 9 | 6
Diarrhea | 5 | 2
Dyspepsia | 3 | 1
Constipation | 2 | 1
Dry Mouth | 2 | 1
HEMATOLOGIC AND LYMPHATIC
Ecchymosis | 2 | 1
METABOLIC AND NUTRITIONAL
Weight Loss | 3 | 2
NERVOUS SYSTEM
Dizziness | 13 | 7
Ataxia | 6 | 1
Nystagmus | 4 | 2
Paresthesia | 4 | 1
NEUROPSYCHIATRIC AND COGNITIVE DYSFUNCTION-ALTERED COGNITIVE FUNCTION
Confusion | 6 | 3
Difficulty Concentrating | 6 | 2
Difficulty with Memory | 6 | 2
Mental Slowing | 4 | 2
NEUROPSYCHIATRIC AND COGNITIVE DYSFUNCTION-BEHAVIORAL ABNORMALITIES (NON-PSYCHOSIS-RELATED)
Agitation/Irritability | 9 | 4
Depression | 6 | 3
Insomnia | 6 | 3
Anxiety | 3 | 2
Nervousness | 2 | 1
NEUROPSYCHIATRIC AND COGNITIVE DYSFUNCTION-BEHAVIORAL ABNORMALITIES (PSYCHOSIS-RELATED)
Schizophrenic/Schizophreniform Behavior | 2 | 0
NEUROPSYCHIATRIC AND COGNITIVE DYSFUNCTION-CNS DEPRESSION
Somnolence | 17 | 7
Fatigue | 8 | 6
Tiredness | 7 | 5
NEUROPSYCHIATRIC AND COGNITIVE DYSFUNCTION-SPEECH AND LANGUAGE ABNORMALITIES
Speech Abnormalities | 5 | 2
Difficulties in Verbal Expression | 2 | <1
RESPIRATORY
Rhinitis | 2 | 1
SKIN AND APPENDAGES
Rash | 3 | 2
SPECIAL SENSES
Diplopia | 6 | 3
Taste Perversion | 2 | 0

Laboratory Tests

Zonisamide increases serum chloride and alkaline phosphatase and decreases serum bicarbonate [see Warnings and Precautions (5.8)], phosphorus, calcium, and albumin.

Other Adverse Reactions in Clinical Trials of Zonisamide Capsules

Zonisamide capsules have been administered to 1,598 individuals during all clinical trials, only some of which were placebo-controlled. The frequencies represent the proportion of the 1,598 individuals exposed to zonisamide capsules who experienced an event on at least one occasion. All events are included except those already listed in the previous table or discussed in [see Warnings and Precautions (5)], trivial events, those too general to be informative, and those not reasonably associated with zonisamide.

Events are further classified within each category and listed in order of decreasing frequency as follows: frequent occurring in at least 1:100 patients; infrequent occurring in 1:100 to 1:1000 patients; rare occurring in fewer than 1:1000 patients.

Body as a Whole: Frequent: Accidental injury, asthenia. Infrequent: Chest pain, flank pain, malaise, allergic reaction, face edema, neck rigidity. Rare: Lupus erythematosus.

Cardiovascular: Infrequent: Palpitation, tachycardia, vascular insufficiency, hypotension, hypertension, thrombophlebitis, syncope, bradycardia. Rare: Atrial fibrillation, heart failure, pulmonary embolus, ventricular extrasystoles.

Digestive: Frequent: Vomiting. Infrequent: Flatulence, gingivitis, gum hyperplasia, gastritis, gastroenteritis, stomatitis, cholelithiasis, glossitis, melena, rectal hemorrhage, ulcerative stomatitis, gastro-duodenal ulcer, dysphagia, gum hemorrhage. Rare: Cholangitis, hematemesis, cholecystitis, cholestatic jaundice, colitis, duodenitis, esophagitis, fecal incontinence, mouth ulceration.

Hematologic and Lymphatic: Infrequent: Leukopenia, anemia, immunodeficiency, lymphadenopathy. Rare: Thrombocytopenia, microcytic anemia, petechia.

Metabolic and Nutritional: Infrequent: Peripheral edema, weight gain, edema, thirst, dehydration. Rare: Hypoglycemia, hyponatremia, lactic dehydrogenase increased, SGOT increased, SGPT increased.

Musculoskeletal: Infrequent: Leg cramps, myalgia, myasthenia, arthralgia, arthritis.

Nervous System: Frequent: Tremor, convulsion, abnormal gait, hyperesthesia, incoordination. Infrequent: Hypertonia, twitching, abnormal dreams, vertigo, libido decreased, neuropathy, hyperkinesia, movement disorder, dysarthria, cerebrovascular accident, hypotonia, peripheral neuritis, reflexes increased. Rare: Dyskinesia, dystonia, encephalopathy, facial paralysis, hypokinesia, hyperesthesia, myoclonus, oculogyric crisis.

Behavioral Abnormalities –Non-Psychosis-Related: Infrequent: Euphoria.

Respiratory: Frequent: Pharyngitis, cough increased. Infrequent: Dyspnea. Rare: Apnea, hemoptysis.

Skin and Appendages: Frequent: Pruritus. Infrequent: Maculopapular rash, acne, alopecia, dry skin, sweating, eczema, urticaria, hirsutism, pustular rash, vesiculobullous rash.

Special Senses: Frequent: Amblyopia, tinnitus. Infrequent: Conjunctivitis, parosmia, deafness, visual field defect, glaucoma. Rare: Photophobia, iritis.

Urogenital: Infrequent: Urinary frequency, dysuria, urinary incontinence, hematuria, impotence, urinary retention, urinary urgency, amenorrhea, polyuria, nocturia. Rare: Albuminuria, enuresis, bladder pain, bladder calculus, gynecomastia, mastitis, menorrhagia.

6.2 Postmarketing Experience

The following serious adverse reactions have been reported since approval and use of zonisamide worldwide. These reactions are reported voluntarily from a population of uncertain size; therefore, it is not possible to estimate their frequency or establish a causal relationship to drug exposure.

Acute pancreatitis, rhabdomyolysis, increased creatine phosphokinase, and drug reaction with eosinophilia and systemic symptoms (DRESS), acute myopia and secondary angle closure glaucoma, and hyperammonemia and encephalopathy [see Warnings and Precautions (5)].

7 DRUG INTERACTIONS

7.1 CNS Depressants

Concomitant use of ZONISADE with other CNS depressants, including alcohol, may increase the risk of CNS depression, as well as other cognitive and/or neuropsychiatric adverse events [see Warnings and Precautions (5.11)].

7.2 Other Carbonic Anhydrase Inhibitors

Concomitant use of ZONISADE, a carbonic anhydrase inhibitor, with any other carbonic anhydrase inhibitor, may increase the severity of metabolic acidosis and may also increase the risk of kidney stone formation [see Warnings and Precautions (5.8, 5.15)]. Therefore, if ZONISADE is given concomitantly with another carbonic anhydrase inhibitor, monitor the patient for the appearance or worsening of metabolic acidosis [see Clinical Pharmacology (12.1, 12.3)].

7.3 CYP3A4 Inducers

If co-administration with a potent CYP3A4 inducer is necessary, the patient should be closely monitored and the dose of ZONISAMIDE and other drugs that CYP3A4 substrates may need to be adjusted [see Clinical Pharmacology (12.3)].

8 USE IN SPECIFIC POPULATIONS

8.1 Pregnancy

Pregnancy Exposure Registry

There is a pregnancy exposure registry that monitors pregnancy outcomes in women exposed to antiepileptic drugs, such as ZONISADE, during pregnancy. To provide information regarding the effects of in utero exposure to ZONISADE, physicians are advised to recommend that pregnant patients taking ZONISADE enroll in the North American Antiepileptic Drug (NAAED) Pregnancy Registry. This can be done by calling the toll-free number 1-888-233-2334 and must be done by patients themselves. Information on the registry can also be found at the website http://www.aedpregnancyregistry.org/.

Risk Summary

Based on findings from animal studies, ZONISADE may cause fetal harm when administered to a pregnant woman. Zonisamide causes metabolic acidosis in humans [see Warnings and Precautions (5.8)]. There are no reports of metabolic acidosis with use of zonisamide in pregnancy; however, there are published prospective cohort studies that suggest an increased rate of small for gestational age infants in pregnancies exposed to zonisamide, which may be associated with metabolic acidosis (see Clinical Considerations and Data).

The available published data from the NAAED Pregnancy Registry has not identified a drug-associated risk of major birth defects with zonisamide use in pregnancy. Although a small prospective cohort study reported an increased risk of major birth defects in zonisamide-exposed pregnancies, this study has methodologic limitations, including small sample size and inability to account for potential confounders (see Data). The available published data pertaining to the use of zonisamide during pregnancy are insufficient to evaluate for a drug-associated risk of miscarriage.

In animal studies, administration of zonisamide during pregnancy produced fetal malformations in multiple species and embryofetal (monkey) or perinatal (rat) death at maternal plasma levels similar to or lower than therapeutic levels in humans [see Warnings and Precautions (5.10) and Data].

The estimated background risk of major birth defects and miscarriage for the indicated population is unknown. All pregnancies have a background risk of birth defect, loss, or other adverse outcomes. In the general U.S. population, the estimated background risk of major birth defects and miscarriage in clinically recognized pregnancies is 2-4% and 15-20%, respectively.

Clinical Considerations

Dose Adjustments During Pregnancy and the Postpartum Period

As with other AEDs, physiological changes during pregnancy may affect zonisamide concentrations and/or therapeutic effect. There have been reports of decreased zonisamide concentrations during pregnancy and restoration of pre-pregnancy concentrations after delivery. Dose adjustments may be necessary to maintain clinical response.

Maternal Adverse Reactions

Metabolic acidosis in pregnancy (due to other causes) may be associated with decreased fetal growth, decreased fetal oxygenation, and fetal death, and may affect the fetus' ability to tolerate labor. There are no reports of metabolic acidosis or fetal death with use of zonisamide in pregnancy [see Warnings and Precautions (5.8)].

Fetal/Neonatal Adverse Reactions

Newborns of mothers treated with zonisamide should be monitored for metabolic acidosis because of transfer of zonisamide to the fetus and possible occurrence of transient metabolic acidosis following birth. Transient metabolic acidosis has been reported in neonates born to mothers treated during pregnancy with a different carbonic anhydrase inhibitor.

Data

Human Data

A prospective cohort study from the NAAED Pregnancy Registry has not identified an increase in the rate of major birth defects (1.4%) in over 200 first trimester pregnancies exposed to zonisamide monotherapy use. Methodological limitations include small sample size and selection bias.

A prospective cohort study from the United Kingdom and Ireland Epilepsy Pregnancy Registry (UKIEPR) reported an increased rate of major birth defects (13%) in 26 first trimester pregnancies exposed to zonisamide monotherapy use. Methodological limitations include small sample size and inability to account for potential confounders.

Prospective cohort studies, including data from NAAED Pregnancy Registry and UKIEPR, have reported increased rates of small for gestational age infants in those exposed to zonisamide during pregnancy compared to lamotrigine-exposed pregnancies and the unexposed general population.

Animal Data

In mice, treatment of pregnant animals with zonisamide (0, 125, 250, or 500 mg/kg/day) during the period of organogenesis resulted in increased incidences of fetal malformations (skeletal and/or craniofacial defects) at all doses tested. A no-effect dose for adverse effects on embryofetal development in mice was not identified. The lowest dose tested was approximately 1.5 times that in humans at the maximum recommended human dose (MRHD) of 400 mg/day on a mg/m^2 basis.

In rats, an increased frequency of malformations (cardiovascular defects) and variations (persistent cords of thymic tissue, decreased skeletal ossification) was observed in the offspring of dams treated with zonisamide (0, 20, 60, or 200 mg/kg/day) throughout organogenesis at all doses. A no-effect dose for adverse effects on embryofetal development in rats was not identified. The lowest dose tested was approximately 0.5 times the MRHD on a mg/m^2 basis.

Following administration of zonisamide (0, 10, 30, or 60 mg/kg/day) to pregnant dogs during organogenesis, increased incidences of fetal cardiovascular malformations (ventricular septal defects, cardiomegaly, various valvular and arterial anomalies) were found at doses of 30 mg/kg/day or greater. Cardiovascular malformations were found in approximately 50% of all fetuses exposed to the high dose. Incidences of skeletal malformations were also increased at the high dose, and fetal growth retardation and increased frequencies of skeletal variations were seen at all doses. Plasma levels in pregnant dogs (12 μg/mL) at the low and mid doses tested (10 and 30 mg/kg, respectively) were lower than those in humans at the MRHD; plasma levels at the high dose tested in pregnant dogs were similar to those in humans at the MRHD.

In cynomolgus monkeys, administration of zonisamide (0, 10 or 20 mg/kg/day) to pregnant animals during organogenesis resulted in embryofetal deaths at both doses. The possibility that these deaths were due to malformations cannot be ruled out. A no-effect dose for embryofetal death was not identified. At the low dose tested, peak plasma levels in pregnant monkey were substantially lower than that in humans at the MRHD.

Perinatal death was increased among the offspring of rats treated with zonisamide (0, 10, 30, or 60mg/kg/day) from the latter part of gestation up to weaning at the high dose. The no-effect dose (30 mg/kg/day) for adverse peri- and postnatal developmental effects in rats is less than the MRHD on a body surface area (mg/m^2) basis.

8.2 Lactation

Risk Summary

Zonisamide is readily transferred to human milk, with a reported milk-to-plasma ratio ranging between 0.7 to 0.9 in the published lactation studies. There are no published reports of adverse effects on the breastfed infant exposed to zonisamide during breastfeeding. There are no data on the effect of zonisamide on milk production. Because ZONISADE has been associated with metabolic acidosis in adult and pediatric patients and hyperthermia in pediatric patients, infants exposed to ZONISADE during breastfeeding should be monitored for poor feeding, weight loss, excess sedation, decreased muscle tone, and elevated temperature [see Warnings and Precautions (5.8)].

The developmental and health benefits of breastfeeding should be considered along with the mother’s clinical need for ZONISADE and any potential adverse effects on the breastfed infant from ZONISADE or from the underlying maternal condition.

8.3 Females and Males of Reproductive Potential

Contraception

Females

Based on animal data, zonisamide can cause fetal harm when administered to a pregnant woman [see Warnings and Precautions (5.10)]. Advise females of reproductive potential to use effective contraception during treatment with ZONISADE and for one month after discontinuation.

Infertility

Females

Based on findings from animal fertility studies, ZONISADE may impair fertility in females [see Nonclinical Toxicology (13.1)].

8.4 Pediatric Use

Safety and effectiveness of ZONISADE have been established in patients 16 years of age and older by evidence from adequate and well-controlled studies of zonisamide [see Clinical Studies (14)].

Safety and effectiveness in pediatric patients below the age of 16 have not been established. Acute myopia and secondary angle closure glaucoma have been reported in pediatric patients [see Warnings and Precautions (5.6)]. Cases of oligohidrosis and hyperpyrexia have been reported [see Warnings and Precautions (5.5)]. Zonisamide commonly causes metabolic acidosis in pediatric patients [see Warnings and Precautions (5.8)]. Chronic untreated metabolic acidosis in pediatric patients may cause nephrolithiasis and/or nephrocalcinosis, osteoporosis and/or osteomalacia (potentially resulting in rickets), and may reduce growth rates. A reduction in growth rate may eventually decrease the maximal height achieved. The effect of zonisamide on growth and bone-related sequelae has not been systematically investigated.

8.5 Geriatric Use

Single dose pharmacokinetic parameters are similar in elderly and young healthy volunteers [see Clinical Pharmacology (12.3)]. Clinical studies of zonisamide did not include sufficient numbers of subjects aged 65 and over to determine whether they respond differently from younger subjects. Other reported clinical experience has not identified differences in responses between the elderly and younger patients. In general, dose selection for an elderly patient should be cautious, usually starting at the low end of the dosing range, reflecting the greater frequency of decreased hepatic, renal, or cardiac function, and of concomitant disease or other drug therapy.

8.6 Renal Impairment

ZONISADE is cleared via renal pathway [see Clinical Pharmacology (12.3)]. Patients with renal impairment might require slower titration, and more frequent monitoring is required. Avoid use of ZONISADE in patients with renal failure (estimated GFR < 50 mL/min). ZONISADE should be discontinued in patients who develop acute renal failure or a clinically significant sustained increase in the creatinine/BUN concentration [see Warnings and Precautions (5.14)].

10 OVERDOSAGE

10.1 Human Experience

During zonisamide clinical development, three patients ingested unknown amounts of zonisamide as suicide attempts, and all three were hospitalized with CNS symptoms. One patient became comatose and developed bradycardia, hypotension, and respiratory depression; the zonisamide plasma level was 100.1 μg/mL measured 31 hours post-ingestion. Zonisamide plasma levels fell with a half-life of 57 hours, and the patient became alert five days later.

10.2 Management

No specific antidotes for zonisamide overdosage are available. Following a suspected recent overdose, emesis should be induced or gastric lavage performed with the usual precautions to protect the airway. General supportive care is indicated, including frequent monitoring of vital signs and close observation.

Zonisamide has a long half-life [see Clinical Pharmacology (12.3)]. Due to the low protein binding of zonisamide (40%), renal dialysis may be effective. The effectiveness of renal dialysis as a treatment of overdose has not been formally studied. A poison control center should be contacted for information on the management of ZONISADE overdosage.

11 DESCRIPTION

ZONISADE (zonisamide oral suspension) is chemically classified as a sulfonamide. The active ingredient is zonisamide, 1,2-benzisoxazole-3-methanesulfonamide. The empirical formula is C8H8N2O3S with a molecular weight of 212.23. Zonisamide is a white powder, pKa = 10.2, and is moderately soluble in water (0.80 mg/mL) and 0.1 N HCl (0.50 mg/mL).

The chemical structure is:

ZONISADE is an aqueous white to off-white liquid oral suspension. Each mL contains 20 mg of zonisamide. Inactive ingredients include carboxymethylcellulose sodium, citric acid monohydrate, microcrystalline cellulose, purified water, sodium benzoate, strawberry flavor, sucralose, trisodium citrate dihydrate, and xanthan gum.

12 CLINICAL PHARMACOLOGY

12.1 Mechanism of Action

The precise mechanism(s) by which zonisamide exerts its anticonvulsant effects is unknown. Zonisamide may produce these effects through action at sodium and calcium channels. In vitro pharmacological studies suggest that zonisamide blocks sodium channels and reduces voltage-dependent, transient inward currents (T-type Ca2+ currents), consequently stabilizing neuronal membranes. Other in vitro studies have demonstrated that zonisamide (10–30 µg/mL) suppresses synaptically-driven electrical activity without affecting postsynaptic GABA or glutamate responses (cultured mouse spinal cord neurons) or neuronal or glial uptake of [^3H]-GABA (rat hippocampal slices). Thus, zonisamide does not appear to potentiate the synaptic activity of GABA. Zonisamide is a carbonic anhydrase inhibitor. The contribution of this pharmacological action to the therapeutic effects of zonisamide is unknown.

12.2 Pharmacodynamics

As a carbonic anhydrase inhibitor, ZONISADE may cause metabolic acidosis and may also increase the risks of hyperammonemia and kidney stone formation [see Warnings and Precautions (5.8, 5.13, 5.15) and Drug Interactions (7.2)].

12.3 Pharmacokinetics

Absorption

Following a 100 mg ZONISADE dose in normal volunteers, the time to maximum plasma concentrations (Tmax) occurred within 0.5–5 hours.

Zonisamide pharmacokinetics are dose-proportional in the range of 200 to 400 mg. Once a stable dose is reached, steady state is achieved within 14 days.

Effect of Food

When ZONISADE is administered with food, the zonisamide Tmax is delayed, occurring at 3.5–7.5 hours, but food has no effect on the bioavailability of zonisamide.

Distribution

The apparent volume of distribution (V/F) of zonisamide is about 1.45 L/kg following a 400 mg oral dose. Zonisamide, at concentrations of 1.0–7.0 mcg/mL, is approximately 40% bound to human plasma proteins. Zonisamide extensively binds to erythrocytes, resulting in an eight-fold higher concentration of zonisamide in red blood cells than in plasma. Protein binding of zonisamide is unaffected in the presence of therapeutic concentrations of phenytoin, phenobarbital, or carbamazepine.

Elimination

The plasma clearance of oral zonisamide is approximately 0.30–0.35 mL/min/kg in patients not receiving enzyme-inducing antiepileptic drugs (AEDs). The clearance of zonisamide is increased to 0.5 mL/min/kg in patients concurrently on enzyme-inducing AEDs (see Potential for Other Drugs to Affect ZONISADE). After a single-dose administration, renal clearance of zonisamide is approximately 3.5 mL/min.

Metabolism

Zonisamide is metabolized by N-acetyl-transferases to form N-acetyl zonisamide and by CYP3A4 to form 2–sulfamoylacetylphenol (SMAP).

Excretion

The elimination half-life of zonisamide in plasma is approximately 63 hours. The elimination half-life of zonisamide in red blood cells is approximately 105 hours. Zonisamide is excreted primarily in urine as parent drug and as the glucuronide of a metabolite. Following multiple dosing, 62% of the radiolabeled dose was recovered in the urine, with 3% in the feces by day 10. Of the excreted dose, 35% was recovered as zonisamide, 15% as N-acetyl zonisamide, and 50% as the glucuronide of SMAP.

Specific Populations

Patients with Renal Impairment

Single 300 mg zonisamide doses were administered to three groups of volunteers. Group 1 was a healthy group with a creatinine clearance ranging from 70–152 mL/min. Group 2 and Group 3 had creatinine clearances ranging from 14.5–59 mL/min and 10–20 mL/min, respectively. Zonisamide renal clearance decreased with decreasing renal function (3.42, 2.50, and 2.23 mL/min, respectively). Marked renal impairment (creatinine clearance < 20 mL/min) was associated with an increase in zonisamide AUC of 35% [see Use in Specific Populations (8.6)].

Patients with Hepatic Impairment

The pharmacokinetics of zonisamide in patients with impaired liver function have not been studied.

Age

The pharmacokinetics of a 300 mg single dose of zonisamide were similar in young (mean age 28 years) and elderly subjects (mean age 69 years).

Drug Interaction Studies

In-Vitro Studies

Enzymes

In vitro studies using human liver microsomes show insignificant (<25%) inhibition of cytochrome P450 isozymes 1A2, 2A6, 2C9, 2C19, 2D6, 2E1, 3A4, 2B6, or 2C8 at zonisamide levels approximately two-fold or greater than clinically relevant unbound serum concentrations. Therefore, ZONISADE is not expected to affect the pharmacokinetics of other drugs via cytochrome P450-mediated mechanisms.

Transporters

An in-vitro study showed that zonisamide is a weak inhibitor of P-gp (MDR1).

In-Vivo Studies

Potential for Zonisamide to Affect Other Drugs

Antiepileptic Drugs

In epileptic patients, steady state dosing with zonisamide capsules resulted in no clinically relevant pharmacokinetic effects on carbamazepine, lamotrigine, phenytoin, or sodium valproate.

Oral Contraceptives

In healthy subjects, steady state dosing with zonisamide capsules did not affect serum concentrations of ethinylestradiol or norethisterone in a combined oral contraceptive.

CYP2D6 Substrates

Coadministration of multiple dosing of zonisamide up to 400 mg/day with single 50-mg doses of desipramine did not significantly affect the pharmacokinetic parameters of desipramine, a probe drug for CYP2D6 activity.

Potential for Other Drugs to Affect ZONISADE

CYP3A4 Inducers

The half-life of zonisamide following a 400 mg dose in patients concurrently on enzyme-inducing AEDs such as phenytoin, carbamazepine, or phenobarbital, was between 27-38 hours; the half-life of zonisamide in patients concurrently on the non-enzyme inducing AED, valproate, was 46 hours.

These effects are unlikely to be of clinical significance when ZONISADE is added to existing therapy; however, changes in zonisamide concentrations may occur if concomitant CYP3A4 inducing antiepileptic or other drugs are withdrawn, dose adjusted or introduced, an adjustment of the ZONISADE dose may be required [see Drug Interactions (7.3)].

CYP3A4 Inhibitors

Steady-state dosing of either ketoconazole (400 mg/day) or cimetidine (1200 mg/day) had no clinically relevant effects on the single dose pharmacokinetics of zonisamide given to healthy subjects.

13 NONCLINICAL TOXICOLOGY

13.1 Carcinogenicity, Mutagenesis, Impairment of Fertility

Carcinogenicity

No evidence of carcinogenicity was found in mice or rats following dietary administration of zonisamide for two years at doses of up to 80 mg/kg/day. In mice, this dose is approximately equivalent to the maximum recommended human dose (MRHD) of 400 mg/day on a mg/m2 basis. In rats, this dose is 1–2 times the MRHD on a mg/m2 basis.

Mutagenesis

Zonisamide was mutagenic in an in vitro chromosomal aberration assay in CHL cells. Zonisamide was not mutagenic or clastogenic in other in vitro assays (Ames, mouse lymphoma tk assay, chromosomal aberration in human lymphocytes) or in the in vivo rat bone marrow cytogenetics assay.

Impairment of Fertility

Rats treated with zonisamide (20, 60, or 200 mg/kg) before mating and during the initial gestation phase showed signs of reproductive toxicity (decreased corpora lutea, implantations, and live fetuses) at all doses. The low dose in this study is approximately 0.5 times the maximum recommended human dose (MRHD) on a mg/m^2 basis.

14 CLINICAL STUDIES

The efficacy of ZONISADE is based upon a bioavailability study comparing ZONISADE oral suspension to zonisamide capsules in healthy subjects. The clinical studies information described below pertains to the zonisamide capsule formulation.

The effectiveness of zonisamide as adjunctive therapy has been established in three multicenter, placebo-controlled, double blind, 3-month clinical trials (two domestic, one European) in 499 patients with refractory partial-onset seizures with or without secondary generalization. Each patient had a history of at least four partial-onset seizures per month in spite of receiving one or two antiepilepsy drugs at therapeutic concentrations. The 499 patients (209 women, 290 men) had a mean age of about 35 years. In the two US studies, over 80% of patients were Caucasian; 100% of patients in the European study were Caucasian. Zonisamide capsules or placebo was added to the existing therapy. The primary measure of effectiveness was median percent reduction from baseline in partial seizure frequency. The secondary measure was proportion of patients achieving a 50% or greater seizure reduction from baseline (responders). The results described below are for all partial seizures in the intent-to-treat populations.

In the first study (n = 203), all patients had a 1-month baseline observation period, then received placebo or zonisamide capsules in one of two dose escalation regimens; either 1) 100 mg/day for five weeks, 200 mg/day for one week, 300 mg/day for one week, and then 400 mg/day for five weeks; or 2) 100 mg/day for one week, followed by 200 mg/day for five weeks, then 300 mg/day for one week, then 400 mg/day for five weeks. This design allowed a 100 mg vs. placebo comparison over weeks 1–5, and a 200 mg vs. placebo comparison over weeks 2–6; the primary comparison was 400 mg (both escalation groups combined) vs. placebo over weeks 8–12. The total daily dose was given as twice a day dosing. Statistically significant treatment differences favoring zonisamide were seen for doses of 100, 200, and 400 mg/day.

In the second (n = 152) and third (n = 138) studies, patients had a 2–3 month baseline, then were randomly assigned to placebo or zonisamide capsules for three months. Zonisamide was introduced by administering 100 mg/day for the first week, 200 mg/day the second week, then 400 mg/day for two weeks, after which the dose could be adjusted as necessary to a maximum dose of 20 mg/kg/day or a maximum plasma level of 40 µg/mL. In the second study, the total daily dose was given as twice a day dosing; in the third study, it was given as a single daily dose. The average final maintenance doses received in the studies were 530 and 430 mg/day in the second and third studies, respectively. Both studies demonstrated statistically significant differences favoring zonisamide for doses of 400–600 mg/day, and there was no apparent difference between once daily and twice daily dosing (in different studies). Analysis of the data (first 4 weeks) during titration demonstrated statistically significant differences favoring zonisamide at doses between 100 and 400 mg/day. The primary comparison in both trials was for any dose over Weeks 5–12.

Table 3. Median % Reduction in All Partial-Onset Seizures and % Responders in Primary Efficacy Analyses: Intent-To-Treat Analysis
Study | Median % Reduction in Partial-Onset Seizures |  | % Responders
 | Zonisamide Capsules | Placebo | Zonisamide Capsules | Placebo
Study 1: | n=98 | n=72 | n=98 | n=72
Weeks 8-12: | 40.5% [p<0.05 compared to placebo] | 9.0% | 41.8% | 22.2%
Study 2: | n=69 | n=72 | n=69 | n=72
Weeks 5-12: | 29.6% | -3.2% | 29.0% | 15.0%
Study 3: | n=67 | n=66 | n=67 | n=66
Weeks 5-12: | 27.2% | -1.1% | 28.0% | 12.0%

Table 4. Median % Reduction in All Partial-Onset Seizures and % Responders for Dose Analyses in Study 1: Intent-To-Treat Analysis
Dose Group | Median % Reduction in Partial-Onset Seizures |  | % Responders
 | Zonisamide Capsules | Placebo | Zonisamide Capsules | Placebo
100-400 mg/day: | n=112 | n=83 | n=112 | n=83
Weeks 1-12: | 32.3% [p<0.05 compared to placebo] | 5.6% | 32.1% | 9.6%
100 mg/day: | n=56 | n=80 | n=56 | n=80
Weeks 1-5: | 24.7% | 8.3% | 25.0% | 11.3%
200 mg/day: | n=55 | n=82 | n=55 | n=82
Weeks 2-6: | 20.4% | 4.0% | 25.5% | 9.8%

In Figure 1, a positive value on the Y-axis indicates an improvement from baseline (i.e., a decrease in seizure rate), while a negative value indicates a worsening from baseline (i.e., an increase in seizure rate). Thus, in a display of this type, the curve for an effective treatment is shifted to the left of the curve for placebo. The proportion of patients achieving any particular level of reduction in seizure rate was consistently higher for the zonisamide groups compared to the placebo groups. For example, Figure 1 indicates that approximately 27% of patients treated with zonisamide experienced a 75% or greater reduction, compared to approximately 12% in the placebo groups.

No differences in efficacy based on age, sex or race, as measured by a change in seizure frequency from baseline, were detected.

16 HOW SUPPLIED/STORAGE AND HANDLING

16.1 How Supplied

ZONISADE (zonisamide oral suspension) is a white to off-white, strawberry flavored liquid containing 100 mg/5 mL zonisamide. It is supplied in a 150 mL amber colored PET bottle with a child resistant cap.

NDC Number: 52652-8001-1

16.2 Storage and Handling

Store at 20°C to 25°C (68°F to 77°F), excursions permitted from 15°C to 30°C (59°F to 86°F) [see USP Controlled Room Temperature]. Protect from light.

Discard unused portion of ZONISADE 30 days after first opening of the bottle.

17 PATIENT COUNSELING INFORMATION

Advise the patient to read the FDA-approved patient labeling (Medication Guide).

Administration

Inform patients that a pharmacist will provide an appropriate device and instructions for measuring the correct dose and that a household teaspoon is not an accurate measuring device. Instruct patients to shake ZONISADE well and discard any unused portion after 30 days of opening the bottle [see Dosage and Administration (2.2)].

Drowsiness

ZONISADE may produce drowsiness, especially at higher doses. Patients should be advised not to drive a car or operate other complex machinery until they have gained experience on ZONISADE sufficient to determine whether it affects their performance. Because of the potential of zonisamide to cause CNS depression, as well as other cognitive and/or neuropsychiatric adverse events, ZONISADE should be used with caution if used in combination with alcohol or other CNS depressants.

Serious Skin Reactions

Patients should contact their physicians immediately if a skin rash develops [see Warnings and Precautions (5.2)].

Acute Myopia and Secondary Angle Closure Glaucoma

Instruct patients to seek immediate medical attention if they experience blurred vision, visual disturbances, or periorbital pain [see Warnings and Precautions (5.6)].

Kidney Stones

Patients should contact their physician immediately if they develop signs or symptoms, such as sudden back pain, abdominal pain, and/or blood in the urine, that could indicate a kidney stone. Increasing fluid intake and urine output may reduce the risk of stone formation, particularly in those with predisposing risk factors for stones [see Warnings and Precautions (5.15)].

Oligohidrosis and Hyperthermia in Pediatric Patients

Patients should contact their physician immediately if a child has been taking ZONISADE and is not sweating as usual with or without a fever [see Warnings and Precautions (5.5)].

Serious Hematologic Events

Because zonisamide can cause hematological complications, patients should contact their physician immediately if they develop a fever, sore throat, oral ulcers, or easy bruising [see Warnings and Precautions (5.3)].

Suicidal Behavior and Ideation

Counsel patients and caregivers that AEDs, including ZONISADE, may increase the risk of suicidal thoughts and behavior and advise them of the need to be alert for the emergence or worsening of symptoms of depression, any unusual changes in mood or behavior, or the emergence of suicidal thoughts, behavior, or thoughts about self-harm. Behaviors of concern should be reported immediately to healthcare providers [see Warnings and Precautions (5.7)].

Hyperammonemia and Encephalopathy

Warn patients about the possible development of hyperammonemia with or without encephalopathy. Although hyperammonemia may be asymptomatic, clinical symptoms of hyperammonemic encephalopathy often include acute alterations in level of consciousness and/or cognitive function with lethargy and/or vomiting. Instruct patients to contact their physician if they develop unexplained lethargy, vomiting, or changes in mental status [see Warnings and Precautions (5.13)].

Metabolic Acidosis

Patients should contact their physician immediately if they develop fast breathing, fatigue/tiredness, loss of appetite, or irregular heartbeat or palpitations, which are possible manifestations of metabolic acidosis [see Warnings and Precautions (5.8)].

Pregnancy

Advise pregnant women and females of reproductive potential of the risk to a fetus. Advise pregnant women to inform their healthcare provider of a known or suspected pregnancy.

Advise women who are exposed to ZONISADE during pregnancy that there is a pregnancy registry that monitors pregnancy outcomes in women exposed to ZONISADE during pregnancy. Encourage patients to report their pregnancy to North American Antiepileptic Drug (NAAED) Pregnancy Registry at 1-888-233-2334 or http://www.aedpregnancyregistry.org/ [see Use in Specific Populations (8.1)].

Lactation

Advise breastfeeding women using ZONISADE to monitor infants for increased sleepiness, decreased appetite, and elevated temperature and to seek medical attention if they notice these signs [see Use in Specific Populations (8.2)].

Manufactured for:
Azurity Pharmaceuticals, Inc.
Woburn, MA 01801

Made in United Kingdom

Patent: https://azurity.com/patents

This product’s labeling may have been updated. For current Full Prescribing Information, please visit www.zonisade.com

PN: 51097-65628-00630
REV#: 02 MAY2025

MEDICATION GUIDE

ZONISADE® (Zaan-i-said)
(zonisamide oral suspension)

What is the most important information I should know about ZONISADE?

- ZONISADE may cause serious skin reactions that can cause death. These serious skin reactions may include a severe rash with blisters and peeling skin, especially around the mouth, nose, eyes and genitals (Stevens-Johnson syndrome). ZONISADE may also cause a rash with blisters and peeling skin over much of the body (toxic epidermal necrolysis). Call your healthcare provider right away if you develop a skin rash.
- ZONISADE can cause blood cell changes such as reduced red and white blood cell counts. Call your healthcare provider right away if you develop fever, sore throat, sores in your mouth, or easy bruising.
- ZONISADE can cause other types of allergic reactions or serious problems that may affect different parts of the body such as your liver, kidneys, heart, or blood cells. You may or may not have a rash with these types of reactions. These reactions can be very serious and can cause death. Call your healthcare provider right away if you have:

- fever
- rash
- swelling of your face
- weakness, fatigue
- severe muscle pain

- swollen lymph glands
- unusual bruising or bleeding
- yellowing of your skin or the white part of your eyes

- ZONISADE may cause decreased sweating and increased body temperature (fever). People, especially children, should be watched for signs of decreased sweating and fever, especially in hot temperatures. Some people may need to be hospitalized for this condition. If you have decreased sweating with or without a fever, call your healthcare provider right away.
- ZONISADE may cause eye problems. Serious eye problems include:
  - any sudden decrease in vision with or without eye pain and redness
  - a blockage of fluid in the eye causing increased pressure in the eye (secondary angle closure glaucoma)

These eye problems can lead to permanent loss of vision if not treated.
Call your healthcare provider right away if you have any new eye symptoms, including any new problems with your vision.

- Like other antiepileptic drugs, ZONISADE may cause suicidal thoughts or actions in a very small number of people, about 1 in 500.

Call a healthcare provider right away if you have any of these symptoms, especially if they are new, worse, or worry you:

- thoughts about suicide or dying
- new or worse depression
- feeling agitated or restless
- trouble sleeping (insomnia)
- acting aggressive, being angry, or violent
- an extreme increase in activity and talking (mania)

- attempt to commit suicide
- new or worse anxiety
- panic attacks
- new or worse irritability
- acting on dangerous impulses
- other unusual changes in behavior or mood

Suicidal thoughts or actions can be caused by things other than medicines. If you have suicidal thoughts or actions, your healthcare provider may check for other causes.
How can I watch for early symptoms of suicidal thoughts and actions?

- Pay attention to any changes, especially sudden changes, in mood, behaviors, thoughts, or feelings.
- Keep all follow-up visits with your healthcare provider as scheduled.
- Call your healthcare provider between visits as needed, especially if you are worried about symptoms.

Do not stop ZONISADE without first talking to a healthcare provider.

- Stopping ZONISADE suddenly can cause serious problems.
- Stopping a seizure medicine suddenly in a patient who has epilepsy can cause seizures that will not stop (status epilepticus).
- ZONISADE can increase the level of acid in your blood (metabolic acidosis). If left untreated, metabolic acidosis can cause brittle or soft bones (osteoporosis, osteomalacia, osteopenia), kidney stones and can slow the rate of growth in children. Metabolic acidosis can happen with or without symptoms. Call your healthcare provider right away if you have any of these symptoms:

- fast breathing
- feel tired
- feel changes in heartbeat

- not feel hungry (loss of appetite)
- have trouble thinking clearly

Your healthcare provider should do a blood test to measure the level of acid in your blood before and during your treatment with ZONISADE.

- ZONISADE may cause problems with thinking and alertness. ZONISADE may affect how you think and cause confusion, problems with concentration, attention, memory, or speech. ZONISADE may cause depression or psychotic symptoms (such as seeing or hearing things that are really not there), tiredness, and sleepiness.
  ZONISADE can have other serious side effects. For more information ask your healthcare provider or pharmacist. Tell your healthcare provider if you have any side effect that bothers you. Be sure to read the section "What are the possible side effects of ZONISADE?”.

What is ZONISADE?

- ZONISADE is a prescription medicine that is used with other medicines to treat partial seizures in adults and children 16 years of age and older.
- It is not known if ZONISADE is safe and effective in children under 16 years of age.

Do not take ZONISADE if you:

- are allergic to sulfonamides or zonisamide.

Before taking ZONISADE, tell your healthcare provider about all your medical conditions, including if you:

- have or have had depression, mood problems or suicidal thoughts or behavior.
- have kidney problems.
- have liver problems.
- have a history of metabolic acidosis (too much acid in your blood).
- have weak, brittle bones or soft bones (osteomalacia, rickets, osteopenia, or osteoporosis).
- have a growth problem.
- are on a diet high in fat called a ketogenic diet.
- have diarrhea.
- have high blood levels of ammonia.
- are pregnant or plan to become pregnant. ZONISADE may harm your unborn baby. Women who can become pregnant should use effective birth control. Tell your healthcare provider right away if you become pregnant or think you may be pregnant while taking ZONISADE. You and your healthcare provider should decide if you should take ZONISADE while you are pregnant.
  There is pregnancy registry for women who are exposed to ZONISADE during pregnancy. If you become pregnant while taking ZONISADE, talk to your healthcare provider about registering with the North American Antiepileptic Drug Pregnancy Registry. You can enroll in this registry by calling 1-888-233-2334. The purpose of this registry is to collect information about the safety of antiepileptic drugs during pregnancy.
- are breastfeeding or plan to breastfeed. ZONISADE can pass into your breast milk. It is not known if ZONISADE in your breast milk can harm your baby. Talk to your healthcare provider about the best way to feed your baby if you take ZONISADE. If you breastfeed while taking ZONISADE, check your baby and call your healthcare provider right away if your baby has increased sleepiness, decreased hunger, or elevated body temperature.

Tell your healthcare provider about all the medicines you take, including prescription and over-the- counter medicines, vitamins, and herbal supplements.

How should I take ZONISADE?

- Take ZONISADE exactly as your healthcare provider tells you to take it.
- ZONISADE is for oral use only.
- Your healthcare prescriber may change your dose. Do not change your dose without talking to your healthcare provider.
- Your pharmacist will provide a measuring device and instructions for measuring the correct dose. Do not use a household teaspoon.
- Take ZONISADE 1 or 2 times each day, with or without food.
- Shake ZONISADE well each time before taking.
- If you take too much ZONISADE, call your local Poison Control Center or go to the nearest emergency room right away.
- Do not stop taking ZONISADE without talking to your healthcare provider. Stopping ZONISADE suddenly can cause serious problems. If you have epilepsy and you stop taking ZONISADE suddenly, you may have an increase in seizures, including seizures that will not stop (status epilepticus).

What should I avoid while taking ZONISADE?

- You should not drink alcohol or take other drugs that make you sleepy or dizzy while taking ZONISADE until you talk to your health care provider. ZONISADE taken with alcohol or drugs that cause sleepiness or dizziness may make your sleepiness or dizziness worse.
- Do not drive a car or operate machinery until you know how ZONISADE affects you. ZONISADE can slow your thinking and motor skills.

What are the possible side effects of ZONISADE?
ZONISADE can cause serious side effects including:
See "What is the most important information I should know about ZONISADE?"

- high blood ammonia levels. High ammonia in the blood can affect your mental status, slow your alertness, make you feel tired, or cause vomiting. Call your healthcare provider right away if you develop unexplained tiredness, vomiting, slow alertness or changes in your mental status.
- kidney stones. Drink plenty of fluids while you take ZONISADE to decrease your chances of getting kidney stones. Call your healthcare provider right away if you get back pain, stomach pain, or blood in your urine.
- decrease in kidney function. ZONISADE may cause a decrease in kidney function. Your healthcare provider should do a blood test to measure your kidney function before and during treatment with ZONISADE.

The most common side effects of ZONISADE include:

- drowsiness
- dizziness
- agitation or irritability

- loss of appetite
- trouble with walking and coordination
- difficulty with memory or concentration

These are not all of the possible side effects of ZONISADE. Call your doctor for medical advice about side effects. You may report side effects to FDA at 1-800-FDA-1088.
You may also report side effects to Azurity Pharmaceuticals, Inc. at 1-800-461-7449.

How should I store ZONISADE?

- Store ZONISADE at room temperature between 68°F to 77°F (20°C to 25°C).
- Protect ZONISADE from light.
- Throw away (discard) any unused ZONISADE 30 days after first opening the bottle.

Keep ZONISADE and all medicines out of the reach of children.

General Information about the safe and effective use of ZONISADE.
Medicines are sometimes prescribed for purposes other than those listed in a Medication Guide. Do not use ZONISADE for a condition for which it was not prescribed. Do not give ZONISADE to other people, even if they have the same symptoms that you have. It may harm them. You can ask your pharmacist or healthcare provider for information about ZONISADE that is written for health professionals.

What are the ingredients in ZONISADE?
Active ingredient: zonisamide
Inactive ingredients: carboxymethylcellulose sodium, citric acid monohydrate, microcrystalline cellulose, purified water, sodium benzoate, strawberry flavor, sucralose, trisodium citrate dihydrate, and xanthan gum.
Manufactured for:
Azurity Pharmaceuticals, Inc.
Woburn, MA 01801 USA

This Medication Guide has been approved by the U.S. Food and Drug Administration. Revised: 06/2025

ZON-MG-02

PRINCIPAL DISPLAY PANEL - Carton Label

NDC 52652-8001-1

ZONISADE®
(zonisamide oral suspension)

100 mg/5 mL

FOR ORAL USE ONLY
SHAKE WELL BEFORE USE

150 mL Rx Only

ATTENTION PHARMACIST:
Dispense Medication Guide to each
patient. Medication Guide available at:
zonisade.com/medication-guide.pdf

azurity® pharmaceuticals